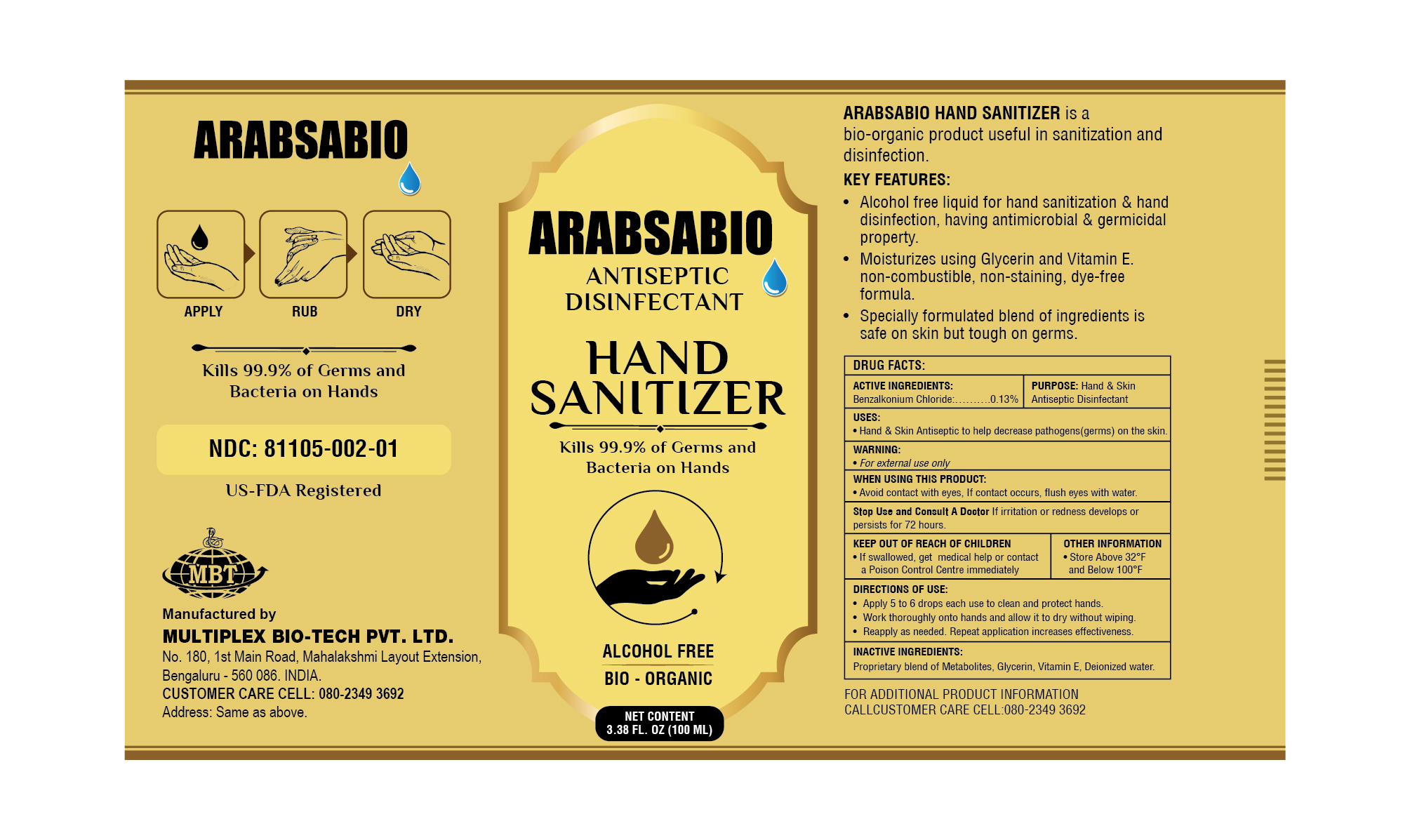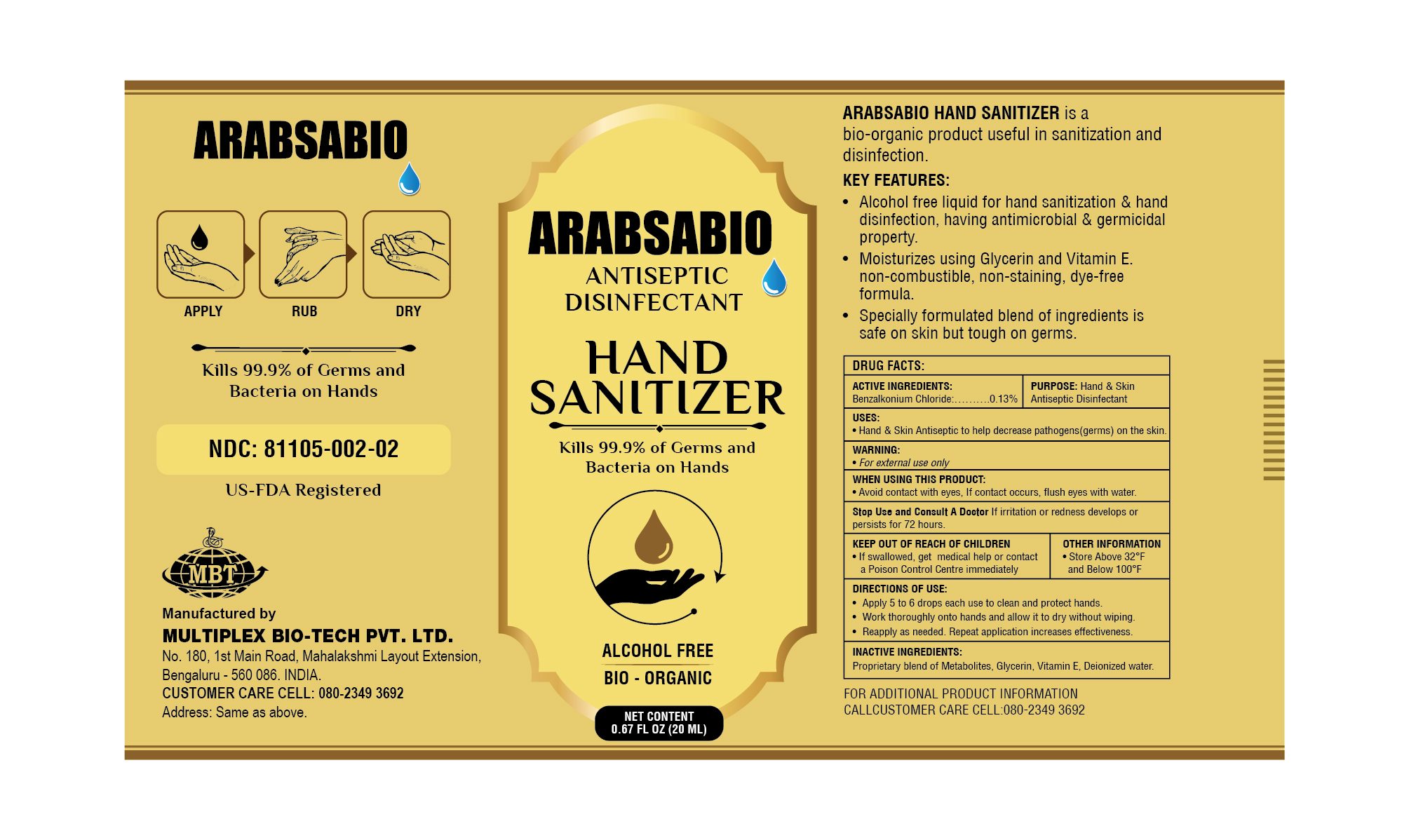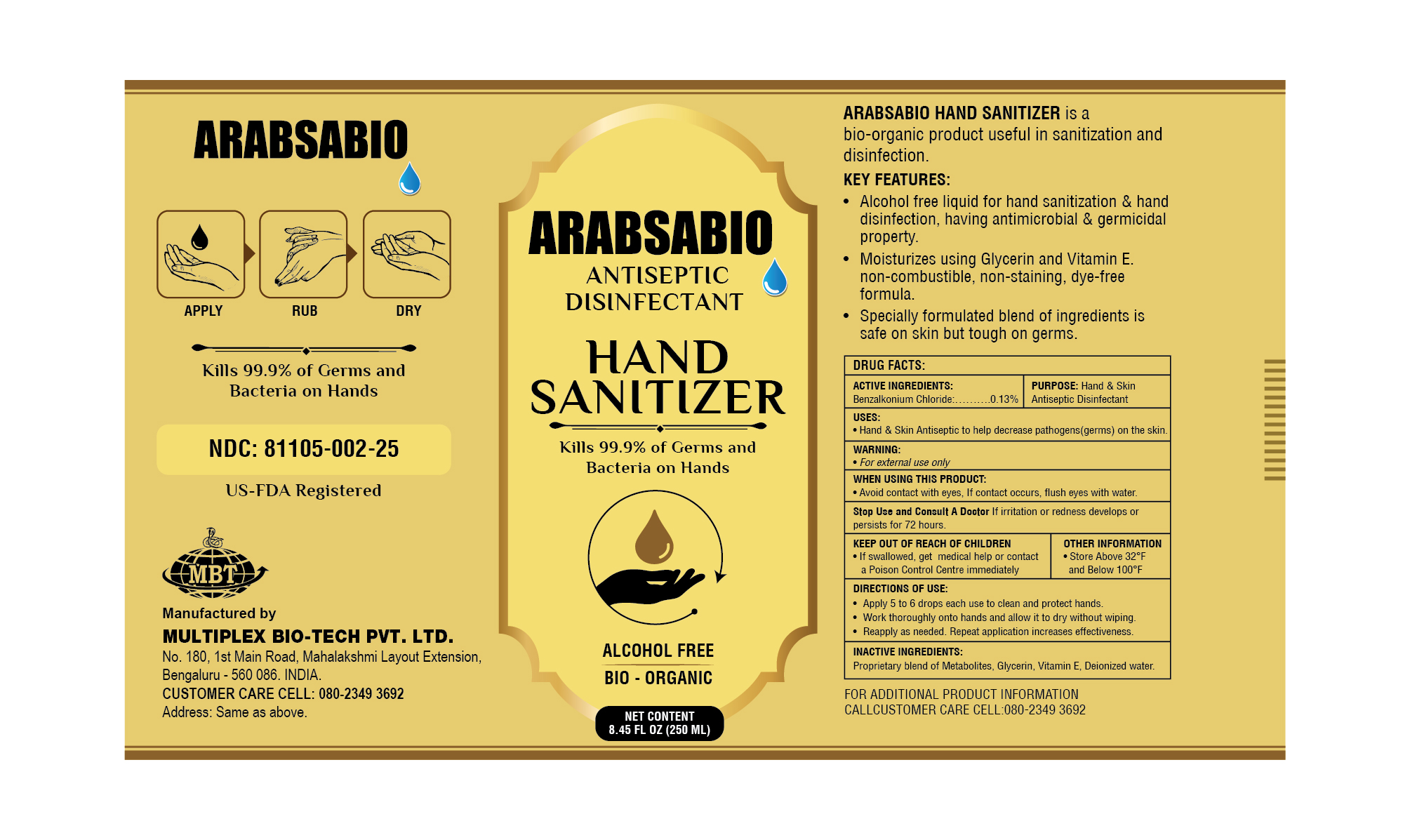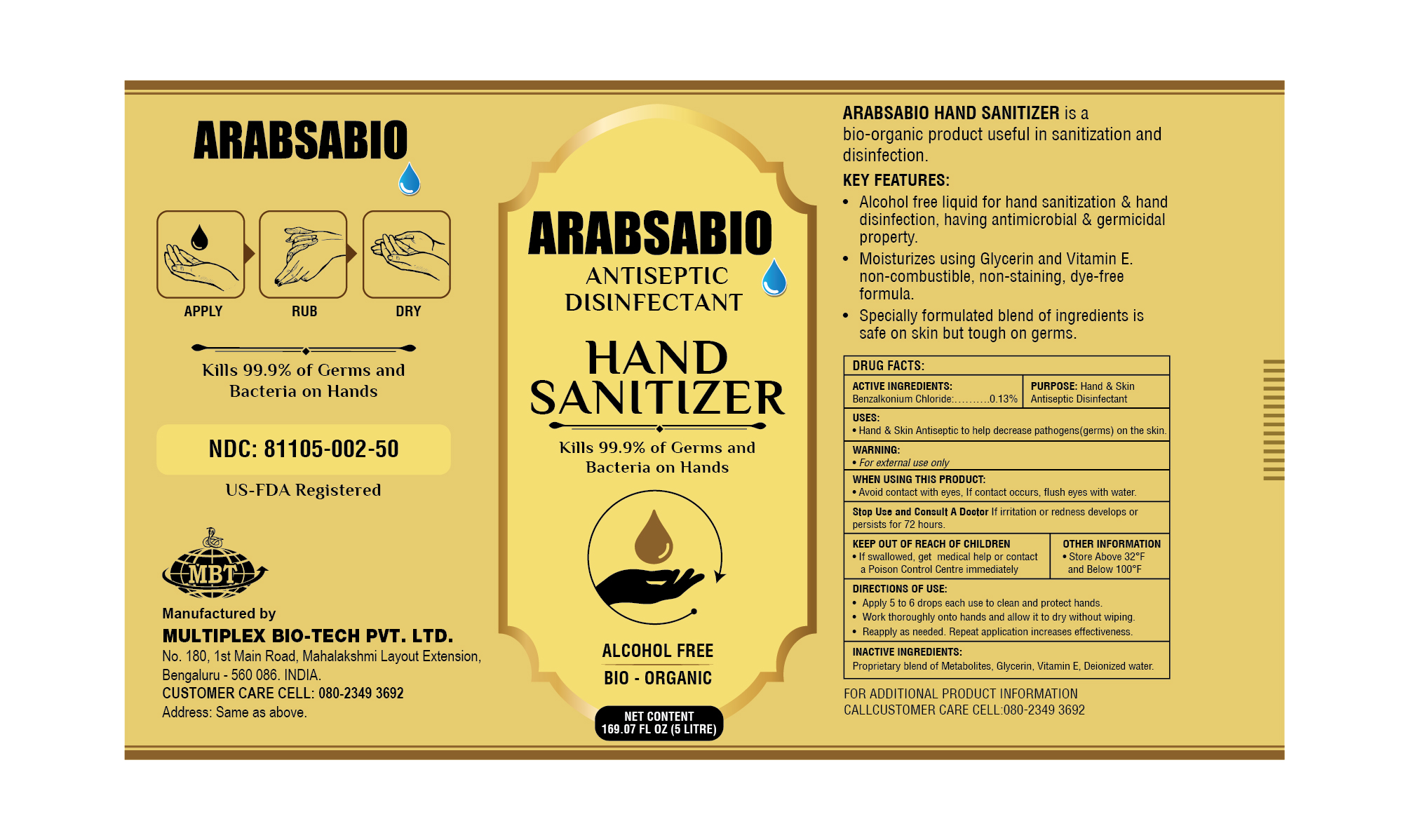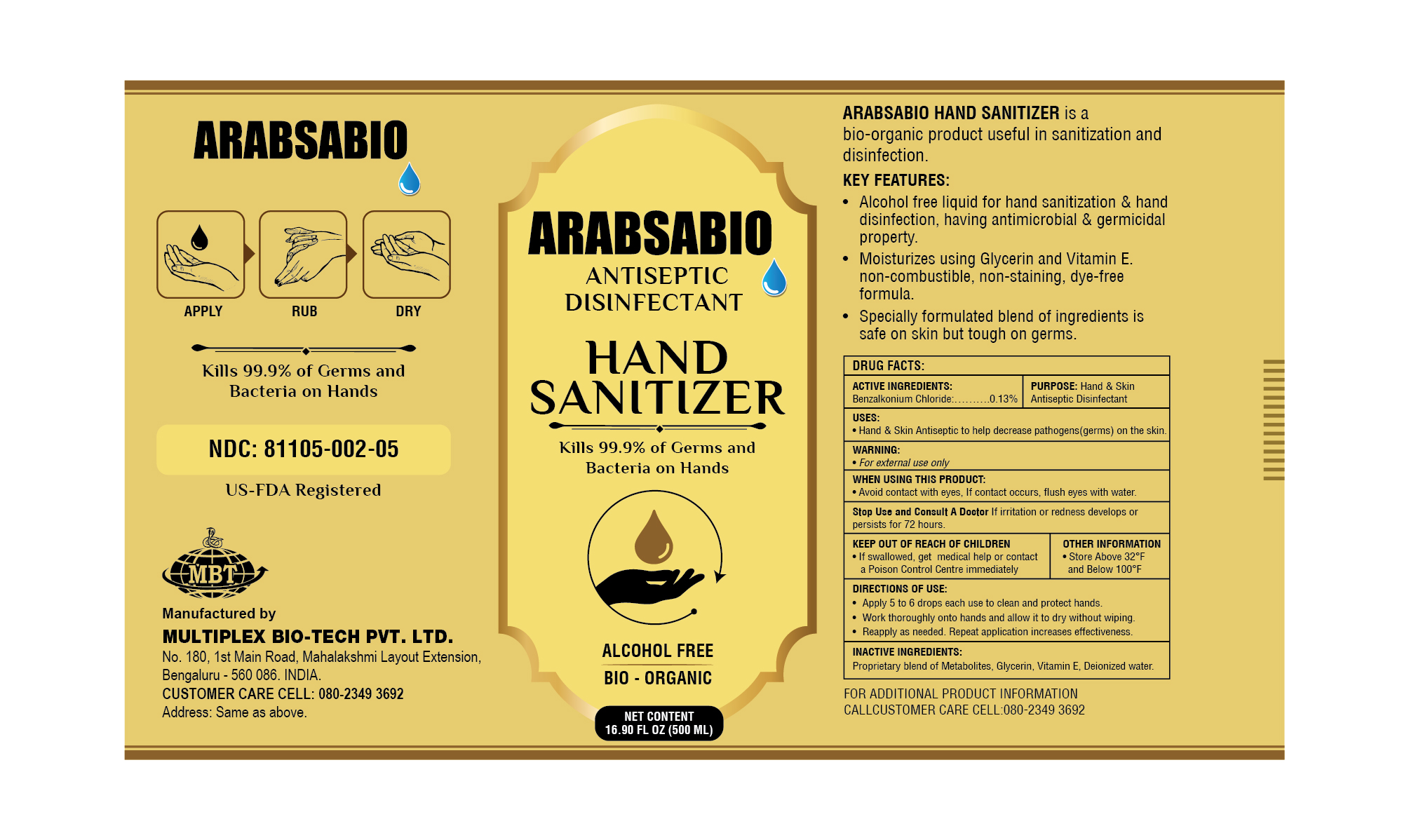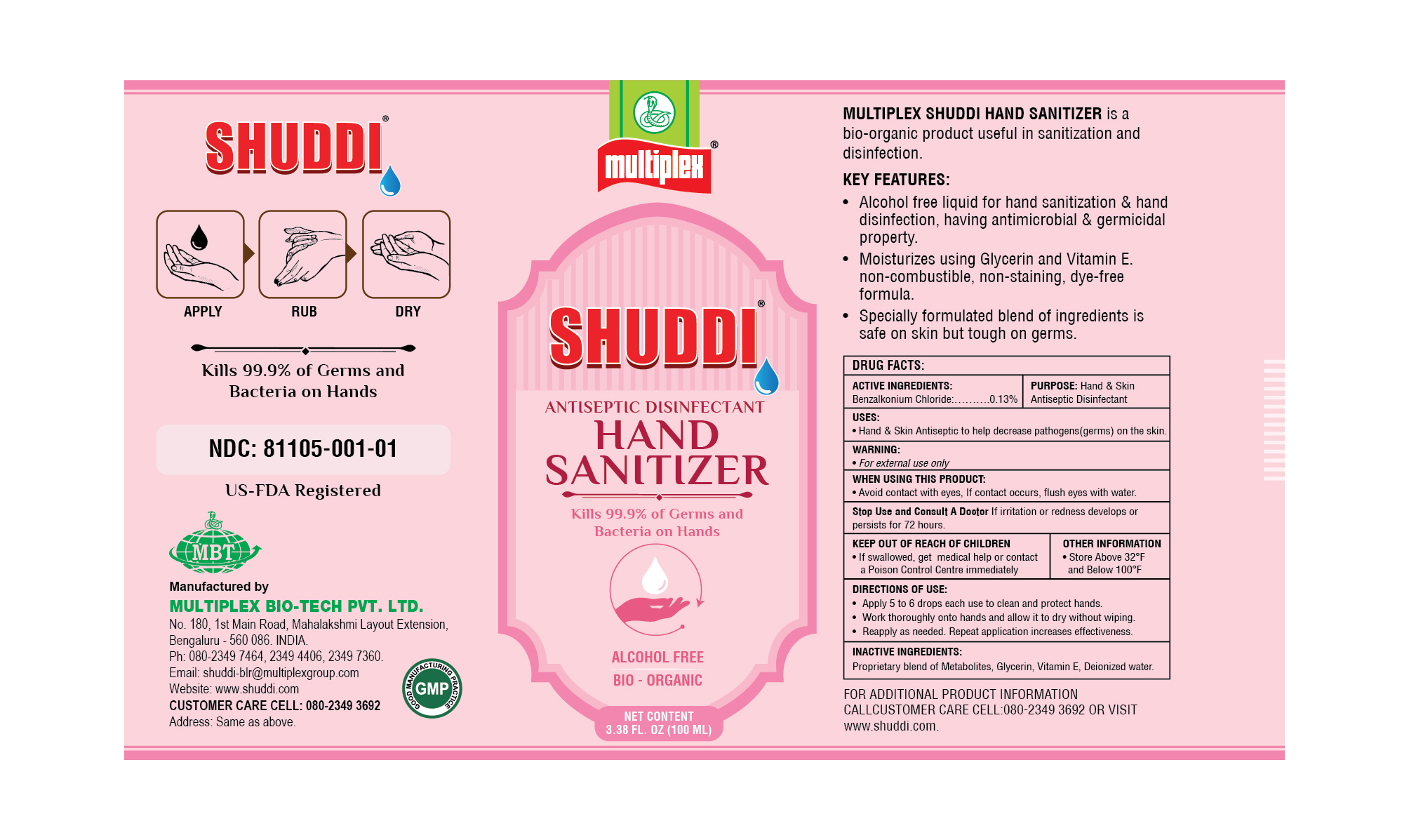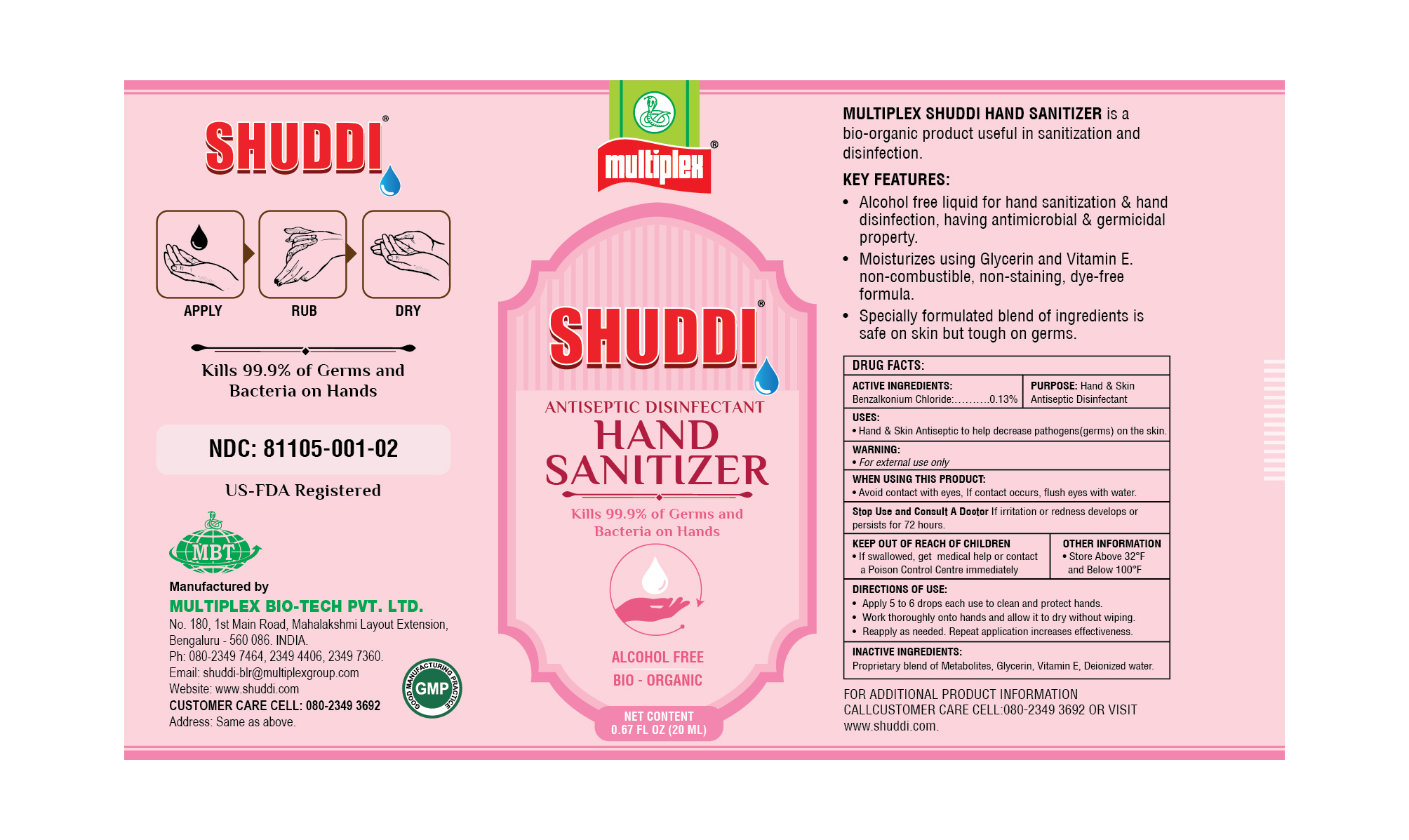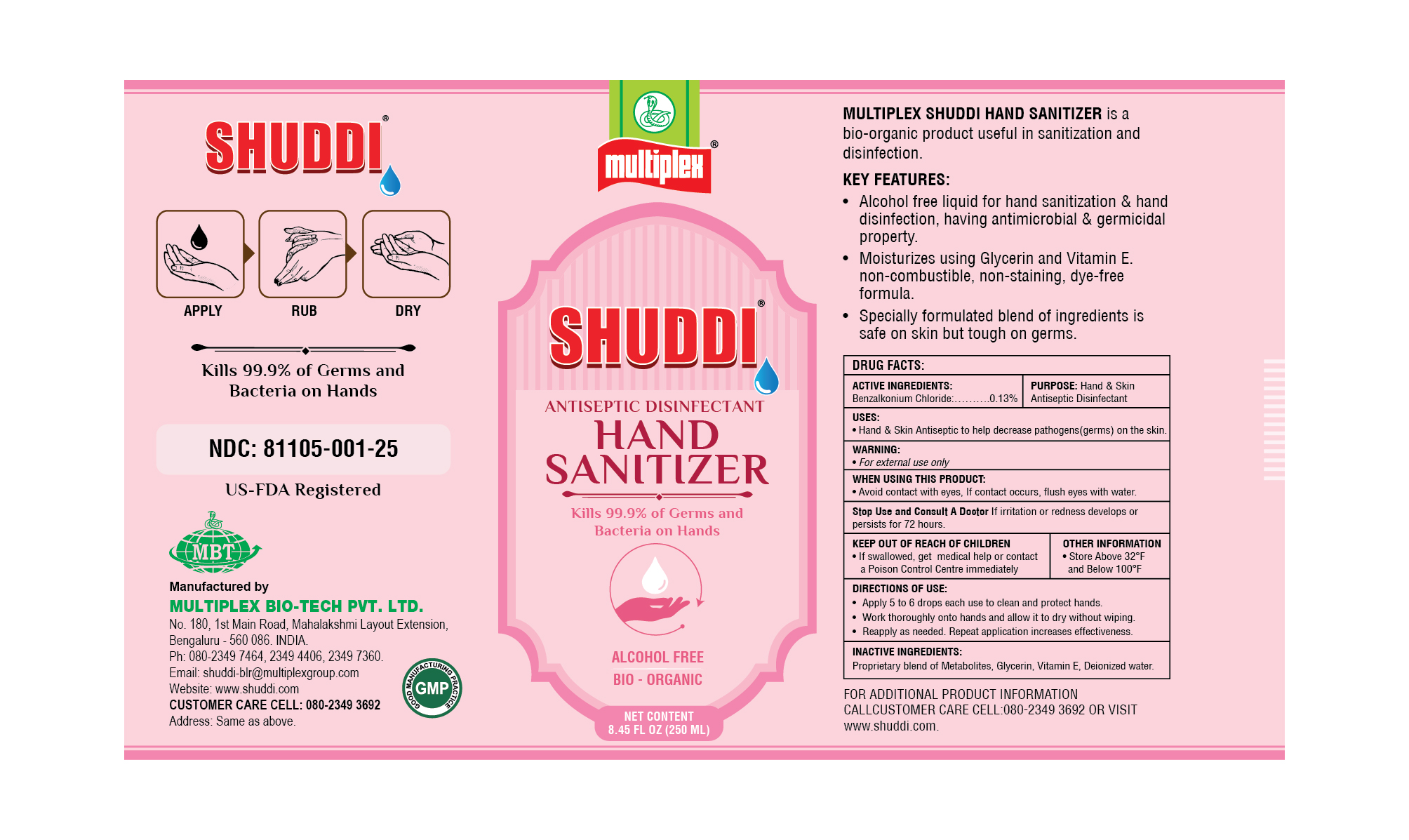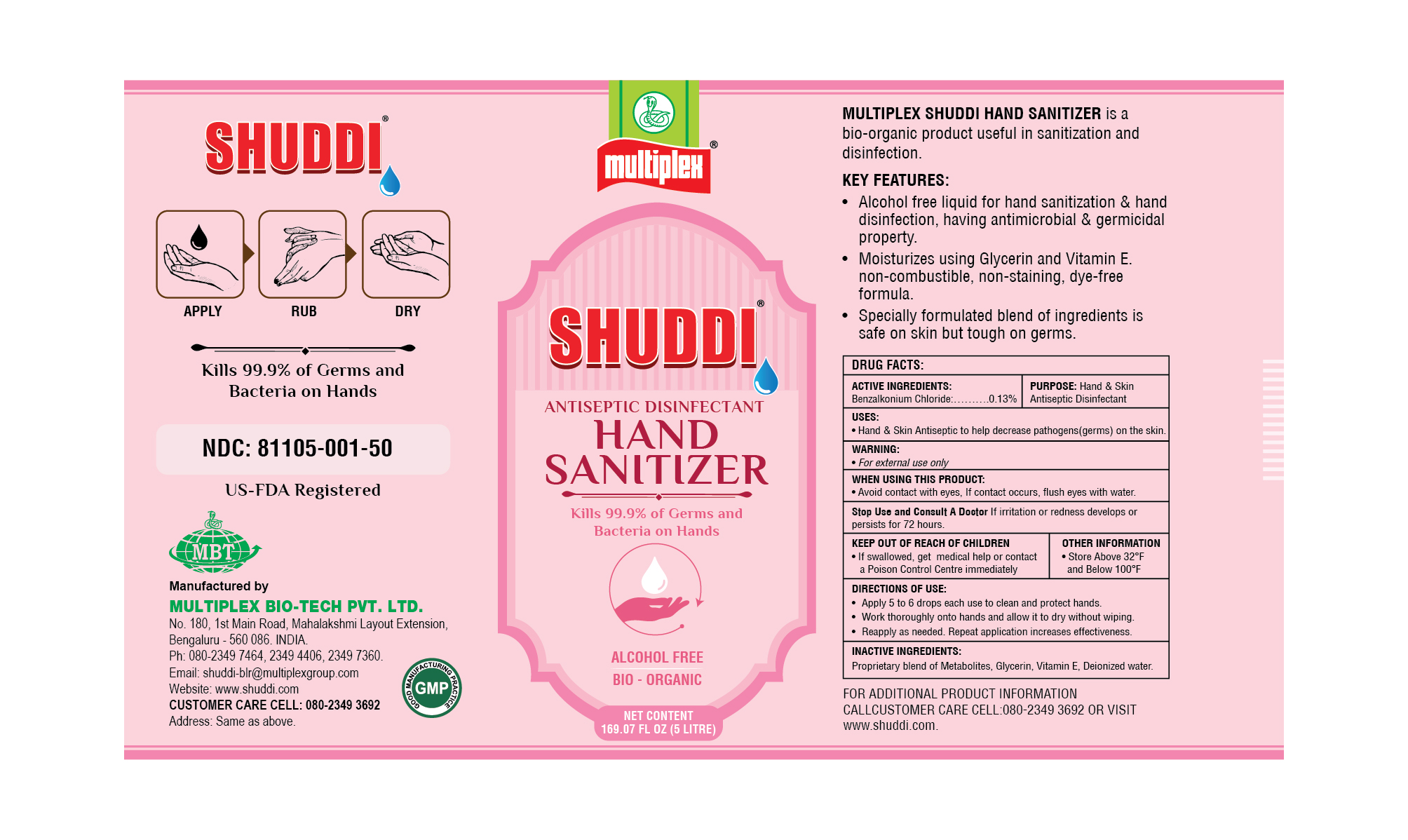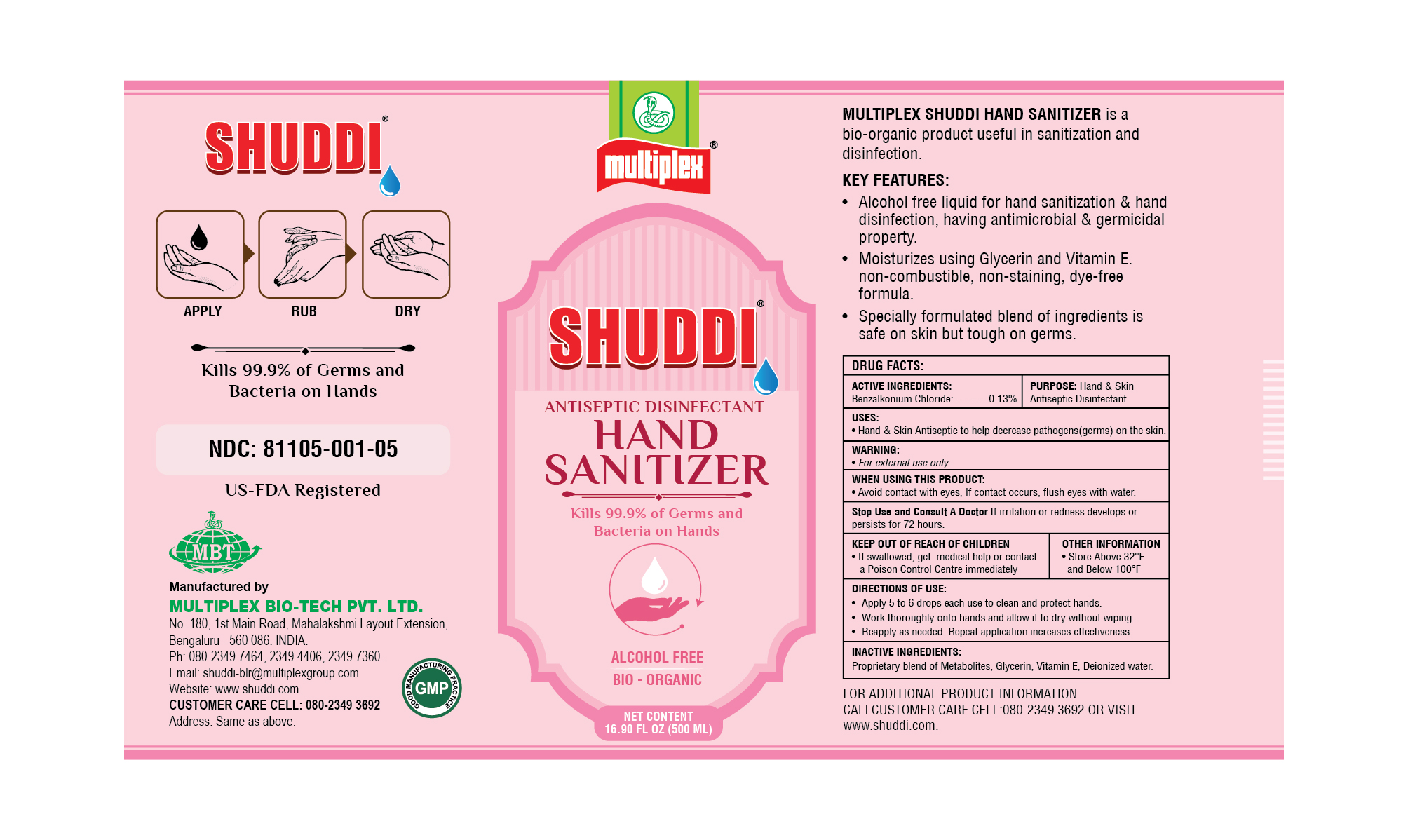 DRUG LABEL: Shuddi Hand Sanitizer
NDC: 81105-001 | Form: LIQUID
Manufacturer: Multiplex Bio-tech Private Limited
Category: otc | Type: HUMAN OTC DRUG LABEL
Date: 20230113

ACTIVE INGREDIENTS: BENZALKONIUM CHLORIDE 0.13 g/100 mL
INACTIVE INGREDIENTS: WATER; .ALPHA.-TOCOPHEROL; GLYCERIN

Drug facts

ACTIVE INGREDIENT

Benzalkonium Chloride 0.13%

PURPOSE

Hand & Skin Antiseptic

INDICATIONS AND USAGE

Hand & Skin Antiseptic to help decrease pathogens (germs) on the skin.

WARNINGS

For external use only.

DO NOT USE

Avoid contact with eyes.

If eye contact occurs, rinse throughly with water.

ASK DOCTOR

If irritation or redness develops or persists for 72 hours.

Children should be supervised when using this product

DOSAGE AND ADMINISTRATION

Apply 5 to 6 drops each use to clearn and protect hands

Work thoroughly onto hands and allow it to dry without wiping

Reapply as needed. Rpeat application increases effectiveness.

INACTIVE INGREDIENT

Glycerin, Vitamin E, Proprietary blend of Metabolites, Deionized water.

QUESTIONS

Call customer care cell: 080-2349-3692

PACKAGE LABEL

Multiplex

Shuddi Antiseptic Disinfectant Hand Sanitizer

Kills 99.9% of Germs and Bacteria on Hands

Alcohol Free Bio-Organic

Multiplex Shuddi Hand sanitizer is a bio-organic product useful in sanitization and disinfection.

Key Features:

* Alcohol free liquid for hand sanitization & hand disinfection, having antimicrobial & germicidal property.

* Moisturizes using Glycerin and Vitamin E. non-combustible, non-staining, dye-free formula.

* Specially formulated blend of ingredients is safe on skin but tough on germs.

Manufactured by

Multiplex Bio-Tech Pvt. Ltd

No. 180, 1st Main Road, Mahalakshmi Layout Extension,

Bengaluru- 560 086. India

Ph.: 080-2349 7464, 2349 4406, 2349 7360

Email: shuddi-blr@multiplexgroup.com

Website: www.shuddi.com

Good Manufacturing Practice (GMP)

Xx fl oz (XX mL) NDC: 81105-001-XX; 81105-002-XX